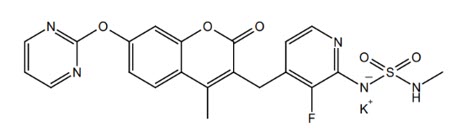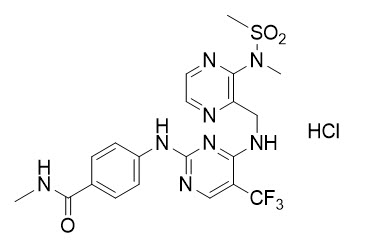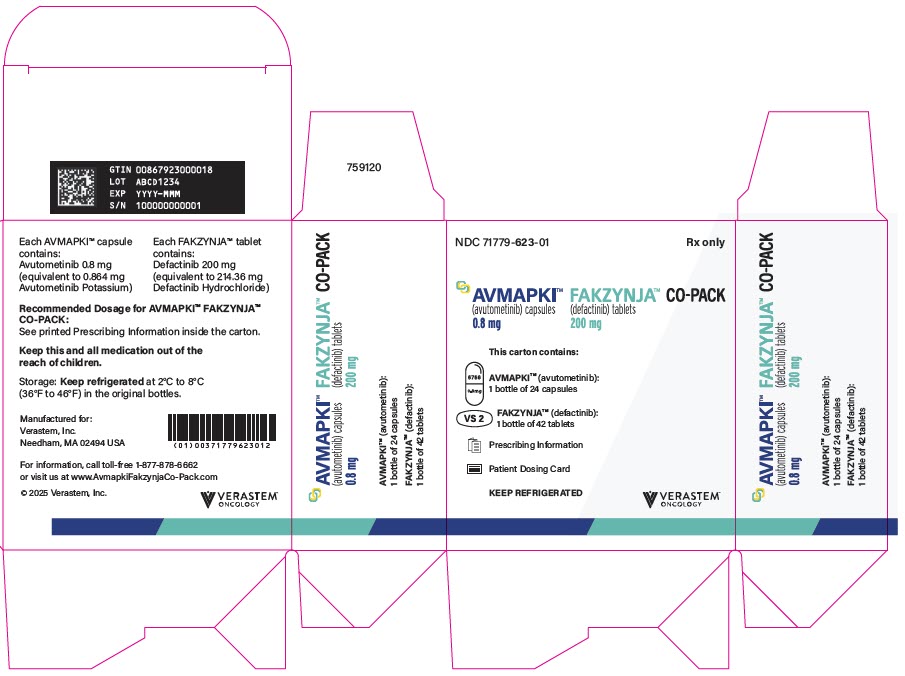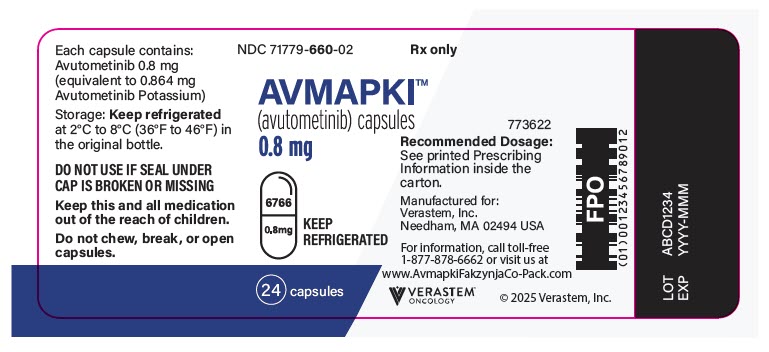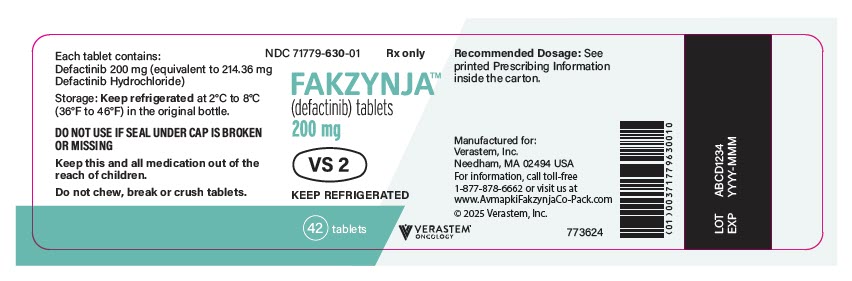 DRUG LABEL: AVMAPKI FAKZYNJA CO-PACK
NDC: 71779-623 | Form: KIT | Route: ORAL
Manufacturer: Verastem Inc.
Category: prescription | Type: HUMAN PRESCRIPTION DRUG LABEL
Date: 20250501

ACTIVE INGREDIENTS: avutometinib potassium 0.8 mg/1 1; defactinib hydrochloride 200 mg/1 1
INACTIVE INGREDIENTS: Mannitol 97.6 mg/1 1; Magnesium stearate 1.5 mg/1 1; HYPROMELLOSE, UNSPECIFIED; Titanium Dioxide; Water; Potassium Chloride; Carrageenan; Shellac; ALCOHOL; Isopropyl Alcohol; Butyl Alcohol; Propylene Glycol; AMMONIA; FERROSOFERRIC OXIDE; Potassium Hydroxide; MICROCRYSTALLINE CELLULOSE 102 368.9 mg/1 1; Lactose monohydrate 184.7 mg/1 1; SODIUM STARCH GLYCOLATE TYPE A 24 mg/1 1; Magnesium stearate 8 mg/1 1

HIGHLIGHTS OF PRESCRIBING INFORMATION

These highlights do not include all the information needed to use AVMAPKI™ FAKZYNJA™ CO-PACK safely and effectively. See full prescribing information for AVMAPKI™ FAKZYNJA™ CO-PACK.
AVMAPKI™ FAKZYNJA™ CO-PACK (avutometinib capsules; defactinib tablets), co-packaged for oral use
Initial U.S. Approval: 2025

1 INDICATIONS AND USAGE

AVMAPKI FAKZYNJA CO-PACK, a combination of avutometinib and defactinib, each kinase inhibitors, is indicated for the treatment of adult patients with KRAS-mutated recurrent low-grade serous ovarian cancer (LGSOC) who have received prior systemic therapy.

This indication is approved under accelerated approval based on tumor response rate and duration of response. Continued approval for this indication may be contingent upon verification and description of clinical benefit in a confirmatory trial. (1,14)

2 DOSAGE AND ADMINISTRATION

- AVMAPKI 3.2 mg administered orally twice weekly (Day 1 and Day 4) for the first 3 weeks of each 4-week cycle. (2.3)
- FAKZYNJA 200 mg administered orally twice daily for the first 3 weeks of each 4-week cycle. (2.3)

3 DOSAGE FORMS AND STRENGTHS

- AVMAPKI Capsules: 0.8 mg of avutometinib (3)
- FAKZYNJA Tablets: 200 mg of defactinib (3)

4 CONTRAINDICATIONS

None. (4)

5 WARNINGS AND PRECAUTIONS

- Ocular Toxicities: Ocular toxicities, including visual impairment and vitreoretinal disorders, occurred. Perform comprehensive ophthalmic evaluation at baseline, prior to cycle 2, every three cycles thereafter, and as clinically indicated. Withhold AVMAPKI FAKZYNJA CO-PACK for ocular toxicities until improvement at the same or reduced dose. Permanently discontinue AVMAPKI FAKZYNJA CO-PACK for any grade 4 toxicity. (2.4, 5.1)
- Serious Skin Toxicities: Skin toxicities, including photosensitivity and severe cutaneous adverse reactions (SCARs), occurred. Adhere to concomitant medications. Monitor for skin toxicities and interrupt, reduce or permanently discontinue AVMAPKI FAKZYNJA CO-PACK based on severity, tolerability and duration. (2.4, 5.2)
- Hepatotoxicity: Monitor liver function tests prior to each cycle, on day 15 of the first 4 cycles, and as clinically indicated. Withhold, reduce or discontinue AVMAPKI FAKZYNJA CO-PACK based on severity and persistence of abnormality. (2.4, 5.3)
- Rhabdomyolysis: Monitor creatine phosphokinase prior to the start of each cycle, on day 15 of the first four cycles, and as clinically indicated. If increased CPK occurs, evaluate patients for rhabdomyolysis or other causes. Withhold, reduce or permanently discontinue AVMAPKI FAKZYNJA CO-PACK based on severity and duration of the adverse reaction. (2.4, 5.4)
- Embryo-Fetal Toxicity: AVMAPKI FAKZYNJA CO-PACK can cause fetal harm. Advise patients of the potential risk to a fetus and to use effective contraception. (5.5, 8.1, 8.3)

6 ADVERSE REACTIONS

The most common (≥ 25%) adverse reactions, including laboratory abnormalities, were increased creatine phosphokinase, nausea, fatigue, increased aspartate aminotransferase, rash, diarrhea, musculoskeletal pain, edema, decreased hemoglobin, increased alanine aminotransferase, vomiting, increased blood bilirubin, increased triglycerides, decreased lymphocyte count, abdominal pain, dyspepsia, dermatitis acneiform, vitreoretinal disorders, increased alkaline phosphatase, stomatitis, pruritus, visual impairment, decreased platelet count, constipation, dry skin, dyspnea, cough, urinary tract infection, and decreased neutrophil count. (6.1)

To report SUSPECTED ADVERSE REACTIONS, contact Verastem at 1-833-633-8786 or FDA at 1-800-FDA-1088 or www.fda.gov/medwatch.

7 DRUG INTERACTIONS

- Strong and moderate CYP3A4 inhibitors: Avoid concomitant use with AVMAPKI FAKZYNJA CO-PACK. (7.1)
- Strong and moderate CYP3A4 inducers: Avoid concomitant use with AVMAPKI FAKZYNJA CO-PACK. (7.1)
- Warfarin: Avoid concomitant use of AVMAPKI FAKZYNJA CO-PACK with warfarin and use an alternative to warfarin. (7.2)
- Gastric acid reducing agents: Avoid concomitant use of AVMAPKI FAKZYNJA CO-PACK with proton pump inhibitors (PPIs) or H2 receptor antagonists. If use of an acid-reducing agent cannot be avoided, administer FAKZYNJA 2 hours before or 2 hours after the administration of a locally acting antacid. (7.1)

8 USE IN SPECIFIC POPULATIONS

Lactation: Advise not to breastfeed. (8.2)

Infertility: May impair fertility in males and females. (8.3)

FULL PRESCRIBING INFORMATION

1 INDICATIONS AND USAGE

AVMAPKI FAKZYNJA CO-PACK is indicated for the treatment of adult patients with KRAS-mutated recurrent low-grade serous ovarian cancer (LGSOC) who have received prior systemic therapy.

This indication is approved under accelerated approval based on tumor response rate and duration of response [see Clinical Studies (14)]. Continued approval for this indication may be contingent upon verification and description of clinical benefit in a confirmatory trial.

2 DOSAGE AND ADMINISTRATION

2.1 Patient Selection

Select patients for the treatment of recurrent LGSOC with AVMAPKI FAKZYNJA CO-PACK based on the presence of a KRAS mutation in tumor specimens [see Clinical Studies (14)].

An FDA-approved test for the detection of a KRAS mutation in LGSOC for selecting patients for treatment with AVMAPKI FAKZYNJA CO-PACK is not available.

2.2 Eye Exams and Prophylactic Skin Medications

Ophthalmic Exams

Conduct a comprehensive ophthalmic exam at baseline, prior to cycle 2, and every three cycles thereafter regardless of baseline exam findings, and as clinically indicated [see Warnings and Precautions (5.1)].

Prophylactic Medications for Skin Reactions

With initiation of and during at least the first 2 cycles of AVMAPKI FAKZYNJA CO-PACK administer [see Warnings and Precautions (5.2)]:

- Topical corticosteroid (applied to the face, scalp, neck, upper chest and upper back)
- Systemic oral antibiotics

2.3 Recommended Dosage and Administration

AVMAPKI Capsules

The recommended dosage of AVMAPKI capsules is 3.2 mg (four 0.8 mg capsules) taken orally twice weekly (Day 1 and Day 4) for the first 3 weeks of each 4-week cycle until disease progression or unacceptable toxicity.

Take AVMAPKI at the same time with each dose. AVMAPKI should be taken with food [see Clinical Pharmacology (12.3)]. Swallow capsules whole. Do not chew, break, or open the capsules.

If a dose of AVMAPKI is missed by more than 24 hours, skip the missed dose and take the next scheduled dose as prescribed. Do not take two doses at the same time to make up for a missed dose. If vomiting occurs after taking AVMAPKI, do not take an additional dose. Take the next scheduled dose as prescribed.

FAKZYNJA Tablets

The recommended dosage of FAKZYNJA tablets is 200 mg (one tablet) taken orally twice daily for the first 3 weeks of each 4-week cycle until disease progression or unacceptable toxicity.

Take each dose of FAKZYNJA with food [see Clinical Pharmacology (12.3)]. Swallow tablets whole. Do not chew, break or crush the tablets.

If a dose of FAKZYNJA is missed by more than 6 hours, skip the missed dose and take the next scheduled dose as prescribed. Do not take two tablets at the same time to make up for a missed dose. If vomiting occurs after taking FAKZYNJA, do not take an additional dose. Take the next scheduled dose as prescribed.

2.4 Dosage Modifications for Adverse Reactions

Dose reductions due to adverse reactions due to AVMAPKI FAKZYNJA CO-PACK are summarized in Table 1.

Table 1 Recommended Dose Reductions for Adverse Reactions
Dose Level | AVMAPKI Capsule | FAKZYNJA Tablet
Starting dose | 3.2 mg twice weekly for first 3 weeks of each 4-week cycle | 200 mg twice daily for first 3 weeks of each 4-week cycle
Dose reduction | 2.4 mg twice weekly for first 3 weeks of each 4-week cycle | 200 mg once daily for first 3 weeks of each 4-week cycle
Permanently discontinue both AVMAPKI and FAKZYNJA in patients unable to tolerate after one dose reduction of both products.

Dosage modifications for adverse reactions to AVMAPKI FAKZYNJA CO-PACK are summarized in Table 2.

Table 2 AVMAPKI FAKZYNJA CO-PACK Dosage Modifications
Adverse Reaction | Severity [Severity as defined by National Center Institute Common Terminology Criteria for Adverse Events (NCI CTCAE) version 5.0] | Dose Modification
Keratitis [see Warnings and Precautions (5.1)] | Confluent superficial keratitis, a cornea epithelial defect, or 3-line or more loss in best corrected distance visual acuity | Withhold AVMAPKI FAKZYNJA CO-PACK until resolved to nonconfluent superficial keratitis, then resume at same dose.
Keratitis [see Warnings and Precautions (5.1)] | Corneal ulcer or stromal opacity or best corrected distance visual acuity 20/200 or worse Corneal perforation | Withhold AVMAPKI FAKZYNJA CO-PACK until resolved to nonconfluence superficial keratitis, then resume at reduced dose. Permanently discontinue AVMAPKI FAKZYNJA CO-PACK.
Blurred vision [see Warnings and Precautions (5.1)] | BCVA worse than baseline but no worse than 20/200 | Withhold AVMAPKI FAKZYNJA CO-PACK until resolution to baseline or 20/40, whichever is worse, then resume treatment at same dose.
Blurred vision [see Warnings and Precautions (5.1)] | BCVA 20/200 or worse | Withhold AVMAPKI FAKZYNJA CO-PACK until resolution to baseline or 20/40, whichever is worse, then resume at reduced dose.
Conjunctivitis [see Warnings and Precautions (5.1)] | Confluent superficial punctate staining, moderate to severe vasodilation | Withhold AVMAPKI FAKZYNJA CO-PACK until resolution to nonconfluent superficial keratitis, then resume at same dose.
Conjunctivitis [see Warnings and Precautions (5.1)] | Conjunctival ulcer or neovascularization | Withhold AVMAPKI FAKZYNJA CO-PACK until resolution to nonconfluent superficial keratitis, then resume at reduced dose.
Retinal Pigment Epithelial (RPE) Detachment [see Warnings and Precautions (5.1)] | N/A | First occurrence; - Repeat Optical Coherence Tomography (OCT) examination in two weeks.; First follow-up OCT examination and RPE present; - Reduce dose of AVMAPKI FAKZYNJA CO-PACK - Repeat OCT examination in two weeks.; Second follow-up OCT examination and RPE present and/or loss of 1 line in BCVA:; - Withhold AVMAPKI FAKZYNJA CO-PACK - Repeat OCT examination in two weeks.; Third follow-up OCT examination; - RPE resolving/resolved, resume at reduced dose. - No resolution, permanently discontinue AVMAPKI FAKZYNJA CO-PACK
Rash [see Warnings and Precautions (5.2)] | Grade ≤ 2 | Consider withholding AVMAPKI FAKZYNJA CO-PACK if rash does not respond to supportive care or recurs after resolution to Grade ≤1. Dose reduce AVMAPKI FAKZYNJA CO-PACK for intolerable Grade 2.
Rash [see Warnings and Precautions (5.2)] | Grade 3 | Withhold AVMAPKI FAKZYNJA CO-PACK until resolved to Grade 2 then resume at reduced dose. Resume at same dose if resolved to Grade ≤1. Permanently discontinue AVMAPKI FAKZYNJA CO-PACK for recurrent Grade 3 despite dose reduction.
Rash [see Warnings and Precautions (5.2)] | Grade 4 | Permanently discontinue AVMAPKI FAKZYNJA CO-PACK.
Hepatotoxicity [see Warnings and Precautions (5.3)] | Grade 2 | Withhold AVMAPKI FAKZYNJA CO-PACK for; - Grade 2 hyperbilirubinemia (without Gilbert's syndrome) with Grade ≤1 increase in AST and/or ALT until hyperbilirubinemia Grade ≤1, then resume at same dose. - Grade 2 hyperbilirubinemia with Grade 2 increase in AST and/or ALT until hyperbilirubinemia Grade ≤1 or baseline, then resume at same dose.; Permanently discontinue AVMAPKI FAKZYNJA CO-PACK for Grade 2 hyperbilirubinemia associated with Grade >2 increase in AST and/or ALT.
Hepatotoxicity [see Warnings and Precautions (5.3)] | Grade 3 | Withhold AVMAPKI FAKZYNJA CO-PACK; - if Grade 3 hyperbilirubinemia is associated with Grade ≤1 increase in AST and/or ALT until hyperbilirubinemia Grade ≤1 or at baseline, then resume at same dose. - if recurrent Grade 3 hyperbilirubinemia is associated with Grade ≤1 increase in AST and/or ALT until hyperbilirubinemia Grade ≤2 or at baseline, then resume at reduced dose. - if Grade 3 increased AST and/or ALT is not associated with hyperbilirubinemia until Grade ≤2 or at baseline, then resume at reduced dose.; Permanently discontinue AVMAPKI FAKZYNJA CO-PACK for Grade 3 hyperbilirubinemia associated with Grade ≥2 increase in AST and/or ALT.
Hepatotoxicity [see Warnings and Precautions (5.3)] | Grade 4 | Withhold AVMAPKI FAKZYNJA CO-PACK for; - Grade 4 hyperbilirubinemia associated with Grade ≤1 increase in AST and/or ALT and if resolves within one week resume at reduced dose.; Permanently discontinue AVMAPKI FAKZYNJA CO-PACK for; - Grade 4 increase in AST and/or ALT. - Grade 4 hyperbilirubinemia associated with Grade ≤1 increase in AST and/or ALT that does not resolve within 1 week.; Grade 4 hyperbilirubinemia associated with Grade ≥2 increase in AST and/or ALT.
Increased Blood Creatine Phosphokinase (CPK) [see Warnings and Precautions (5.4)] | Grade 3 | Withhold AVMAPKI FAKZYNJA CO-PACK, if improves to Grade ≤1 within three weeks resume at same dose. Permanently discontinue AVMAPKI FAKZYNJA CO-PACK for CPK elevation longer than three weeks.
Increased Blood Creatine Phosphokinase (CPK) [see Warnings and Precautions (5.4)] | Grade 4 | Withhold AVMAPKI FAKZYNJA CO-PACK, if improves to Grade ≤1 within three weeks resume at reduced dose. Permanently discontinue AVMAPKI FAKZYNJA CO-PACK for CPK elevation longer than three weeks.
Increased Blood Creatine Phosphokinase (CPK) [see Warnings and Precautions (5.4)] | Any grade CPK elevation with rhabdomyolysis or other event related to CPK elevation | Permanently discontinue AVMAPKI FAKZYNJA CO-PACK
Other Adverse Reactions | Grade 2 | Consider withholding AVMAPKI FAKZYNJA CO-PACK if adverse reaction does not respond to supportive care or recurs after resolution to Grade ≤1.
Other Adverse Reactions | Grade 3 | First occurrence: Withhold AVMAPKI FAKZYNJA CO-PACK until resolved to baseline or Grade ≤1 then resume at same dose. Second occurrence: Withhold AVMAPKI FAKZYNJA CO-PACK until resolved to baseline or Grade ≤1 then resume at reduced dose. Permanently discontinue AVMAPKI FAKZYNJA CO-PACK for recurrent Grade 3 despite dose reduction.
Other Adverse Reactions | Grade 4 | Permanently discontinue AVMAPKI FAKZYNJA CO-PACK.
N/A: Not applicable

3 DOSAGE FORMS AND STRENGTHS

AVMAPKI FAKZYNJA CO-PACK is AVMAPKI (avutometinib) capsules co-packaged with FAKZYNJA (defactinib) tablets.

- AVMAPKI capsules contain 0.8 mg avutometinib and are white capsules with "6766" printed on the cap and the strength "0.8 mg" printed on the body in black ink.
- FAKZYNJA tablets contain 200 mg defactinib and are white to off-white tablets, oval and debossed with "VS2" on one side.

4 CONTRAINDICATIONS

None.

5 WARNINGS AND PRECAUTIONS

5.1 Ocular Toxicities

AVMAPKI FAKZYNJA CO-PACK can cause ocular adverse reactions, including visual impairment and vitreoretinal disorders.

Ocular adverse reactions occurred in 68% of patients with recurrent LGSOC treated with AVMAPKI FAKZYNJA CO-PACK. Common ocular adverse reactions (≥ 5%) were visual impairment (38%), dry eye (13%), orbital/periorbital edema (8%), and vitreous floaters (5%). Thirty-five patients (26%) experienced vitreoretinal disorders, including retinal detachment (9%), and retinal vein occlusion (0.7%). Eighteen patients (13%) experienced an ocular adverse reaction that resulted in dose interruption of AVMAPKI FAKZYNJA CO-PACK and one patient experienced an ocular adverse reaction that resulted in dose reduction.

The median time to onset of symptomatic ocular adverse reactions was 5 days (range 1 to 943 days) and to onset of asymptomatic ocular adverse reactions was 112 days (range 23 to 943 days). The median time to onset of retinal detachment was 27 days (range 2 to 535 days). Of the patients who experienced ocular adverse reactions, 29% had ongoing ocular events at last follow-up.

Refer patients to a qualified eye care professional for a comprehensive ophthalmic exam at baseline, prior to cycle 2, every three cycles thereafter, and as clinically indicated. Promptly refer patients to an eye care professional for any new or worsening ocular signs or symptoms.

Monitor for ocular adverse reactions and withhold, reduce, or permanently discontinue AVMAPKI FAKZYNJA CO-PACK based on severity and persistence of ocular adverse reactions [see Dosage and Administration (2.4)].

5.2 Serious Skin Toxicities

AVMAPKI FAKZYNJA CO-PACK can cause serious skin toxicities, including Severe Cutaneous Adverse Reactions (SCARs). Cases of acute generalized exanthematous pustulosis, erythema multiforme and drug reaction with eosinophilia and systemic symptoms have been reported in clinical trials of avutometinib (a drug in AVMAPKI FAKZYNJA CO-PACK).

Skin toxicities occurred in 94% of patients with recurrent LGSOC treated with AVMAPKI FAKZYNJA CO-PACK. The most common skin toxicities (≥ 10%) were rash (67%), dermatitis acneiform (43%), dry skin (43%), pruritus (32%), and photosensitivity (13%). Grade 3 skin reactions occurred in 12% of patients including dermatitis acneiform (7%), rash (7%), and pruritus (1.5%). Thirteen patients (10%) developed bacterial skin infections. Skin toxicity led to dose interruption of AVMAPKI FAKZYNJA CO-PACK in 10%, to dose reduction in 7%, and to permanent discontinuation in 0.7% of patients. The median time to onset of the first skin toxicity was 14 days (range 1 to 500 days). At last follow-up, 66% of patients had ongoing skin toxicity.

Patients in RAMP-201 used topical corticosteroids (applied to the face, scalp, neck, upper chest and upper back) and systemic oral antibiotics for prophylaxis of skin adverse reactions. These medications were initiated at the start of AVMAPKI FAKZYNJA CO-PACK and administered during at least the first two cycles of treatment.

Limit unnecessary exposure to sunlight and apply daily sunscreen (sun protection factor [SPF] ≥ 30). Monitor for skin toxicity and withhold, reduce dose, or permanently discontinue AVMAPKI FAKZYNJA CO-PACK based on severity and persistence [see Dosage and Administration (2.4)].

5.3 Hepatotoxicity

AVMAPKI FAKZYNJA CO-PACK can cause hepatotoxicity.

In patients with recurrent LGSOC who received AVMAPKI FAKZYNJA CO-PACK, increased AST (73%), bilirubin (51%), ALT (49%), and alkaline phosphatase (46%) occurred. Grade 3-4 elevations in ALT was 3%, AST was 3%, bilirubin was 2.3% and alkaline phosphatase was 0.8%. Elevations in one or more liver related laboratory values led to dose interruption for 20%, dose reduction for 2.2%, and permanent discontinuation for 0.7% of patients.

Increased blood bilirubin may be attributed to defactinib (a component of AVMAPKI FAKZYNJA CO-PACK) due to the inhibition of enzymes responsible for metabolizing (uridine diphosphate-glucuronosyltransferase (UGT)1A1) and transporting (Organic Anion Transporting Polypeptides (OATP)1B1/1B3) bilirubin [see Clinical Pharmacology (12.3)].

Monitor liver related laboratory values prior to the start of each cycle, on day 15 of the first four cycles, and as clinically indicated. Withhold, reduce dose, or permanently discontinue AVMAPKI FAKZYNJA CO-PACK based on severity and duration of these adverse reactions [see Dosage and Administration (2.4)].

5.4 Rhabdomyolysis

AVMAPKI FAKZYNJA CO-PACK can cause increased creatine phosphokinase (CPK). Increased CPK occurred in 75% of patients with recurrent LGSOC treated with AVMAPKI FAKZYNJA CO-PACK, including Grade 3-4 elevations in 18% of patients. Among the patients who experienced an elevation in CPK, concurrent increase in creatinine occurred in 19% (n=19/102) and myalgia occurred in 10% (n=10/102). Elevation of CPK >10 times the baseline value with a concurrent increase in serum creatinine of ≥1.5 times the baseline value occurred in 0.7% of patients. Increased CPK resulted in dose interruption for 22%, in dose reduction for 7%, and in discontinuation for 2.9% of patients. Rhabdomyolysis has occurred in a patient with LGSOC treated with AVMAPKI FAKZYNJA CO-PACK at the recommended dosage in a clinical trial.

Monitor CPK prior to the start of each cycle, on day 15 of the first four cycles, and as clinically indicated. If increased CPK occurs, evaluate patients for rhabdomyolysis or other causes. Withhold, reduce or permanently discontinue AVMAPKI FAKZYNJA CO-PACK based on severity and duration of the adverse reactions [see Dose Modifications (2.4)].

5.5 Embryo-Fetal Toxicity

Based on the mechanisms of action, AVMAPKI FAKZYNJA CO-PACK can cause fetal harm when administered to a pregnant woman [see Clinical Pharmacology (12.1)]. Inhibition of either molecular pathway has been associated with embryo-fetal anomalies and lethality in animals.

Advise pregnant women and females of reproductive potential of the potential risk to a fetus. Advise females of reproductive potential to use effective contraception during treatment with AVMAPKI FAKZYNJA CO-PACK and for 1 month after the last dose. Advise male patients with female partners of reproductive potential to use effective contraception during treatment with AVMAPKI FAKZYNJA CO-PACK and for 4 months after the last dose [see Use in Specific Populations (8.3)].

6 ADVERSE REACTIONS

The following adverse reactions are discussed in more detail in other sections of the labeling:

- Ocular Toxicities [see Warnings and Precautions (5.1)]
- Serious Skin Toxicities [see Warnings and Precautions (5.2)]
- Hepatotoxicity [see Warnings and Precautions (5.3)]
- Rhabdomyolysis [see Warnings and Precautions (5.4)]

6.1 Clinical Trials Experience

Because clinical trials are conducted under widely varying conditions, adverse reaction rates observed in the clinical trials of a drug cannot be directly compared to rates in the clinical trials of another drug and may not reflect the rates observed in practice.

The pooled safety population described in Warnings and Precautions reflect exposure to the AVMAPKI FAKZYNJA CO-PACK (combination of AVMAPKI 3.2 mg twice weekly and FAKZYNJA 200 mg twice daily) for the first 3 weeks in a 4-week cycle until disease progression or unacceptable toxicity in 136 adult patients with recurrent LGSOC treated on RAMP-201 and FRAME (NCT03875820). The median duration of treatment was 10 months (range 0 to 51 months).

RAMP-201

The safety of AVMAPKI FAKZYNJA CO-PACK was evaluated in RAMP-201, a single-arm multicenter trial in 57 patients with KRAS-mutated recurrent LGSOC [see Clinical Studies (14)]. Patients received AVMAPKI FAKZYNJA CO-PACK (AVMAPKI 3.2 mg twice weekly and FAKZYNJA 200 mg twice daily) for the first 3 weeks in a 4-week cycle until disease progression or unacceptable toxicity. The median duration of treatment was 12 months (range 0.03-40).

Serious adverse reactions occurred in 32% of patients who received AVMAPKI FAKZYNJA CO-PACK. The most common (≥2%) serious adverse reactions were sepsis (9%), intestinal obstruction (3.6%), pyelonephritis (3.6%), and hydronephrosis (3.6%). Fatal adverse reactions occurred in 3.6% of patients who received AVMAPKI FAKZYNJA CO-PACK, including intestinal obstruction (1.8%) and perforation (1.8%).

Permanent discontinuation of AVMAPKI FAKZYNJA CO-PACK due to an adverse reaction occurred in 14% of patients. The adverse reactions leading to permanent discontinuation included elevations in creatine phosphokinase, dyspnea, malaise, decreased glomerular filtration rate, hyperbilirubinemia, increased alanine aminotransferase, and abdominal pain (1.8% each).

Dosage interruptions of AVMAPKI FAKZYNJA CO-PACK due to an adverse reaction occurred in 84% of patients. Adverse reactions which required dosage interruptions in ≥ 5% of patients included elevations in creatine phosphokinase (25%), hyperbilirubinemia (25%), diarrhea (12%), edema (11%), fatigue (9%), vision blurred (9%), vitreoretinal disorders (7%), transaminitis (7%), paronychia (5%), nausea (5%), abdominal pain (5%), vomiting (5%), dyspnea (5%), sepsis (5%), and rash (5%).

Dose reductions of AVMAPKI FAKZYNJA CO-PACK due to an adverse reaction occurred in 44% of patients. Adverse reactions which required dose reductions in ≥ 5% of patients were elevations in creatine phosphokinase (9%), fatigue (5%), hyperbilirubinemia (5%), and dermatitis acneiform (5%).

The most common (≥25%) adverse reactions, including laboratory abnormalities, were increased creatine phosphokinase, nausea, fatigue, increased aspartate aminotransferase, rash, diarrhea, musculoskeletal pain, edema, decreased hemoglobin, increased alanine aminotransferase, vomiting, increased blood bilirubin, increased triglycerides, decreased lymphocyte count, abdominal pain, dyspepsia, dermatitis acneiform, vitreoretinal disorders, increased alkaline phosphatase, stomatitis, pruritus, visual impairment, decreased platelet count, constipation, dry skin, dyspnea, cough, urinary tract infection, and decreased neutrophil count.

Table 3 summarizes the adverse reactions in RAMP-201.

Table 3 Adverse Reactions (≥10%) in Patients with KRAS-Mutated Recurrent LGSOC who Received AVMAPKI FAKZYNJA CO-PACK in RAMP-201 [Severity as defined by National Center Institute Common Terminology Criteria for Adverse Events (NCI CTCAE) version 5.0.]
Adverse Reaction | AVMAPKI FAKZYNJA CO-PACK N = 57
 | All Grades % | Grade 3 or 4 [No Grade 4 treatment-emergent adverse events occurred.] %
Gastrointestinal disorders
Nausea | 74 | 1.8
Diarrhea | 68 | 7
Vomiting | 49 | 3.5
Abdominal pain [Includes multiple terms] | 39 | 1.8
Dyspepsia | 37 | 0
Stomatitis | 35 | 3.5
Constipation | 30 | 0
Dry mouth | 18 | 0
Decreased Weight | 11 | 0
General disorders and administration site condition
Fatigue | 72 | 3.5
Edema | 67 | 1.8
Skin and subcutaneous tissue disorders
Rash [Includes: butterfly rash, dermatitis, drug eruption, erythema, rash, rash erythematous, rash macular, rash maculo-papular, rash papular, and rash pruritic] | 72 | 3.5
Dermatitis acneiform [Includes: acne, dermatitis acneiform, folliculitis, perioral dermatitis, and rash pustular] | 37 | 5.3
Pruritus | 35 | 1.8
Dry skin | 30 | 0
Alopecia | 23 | 0
Photosensitivity | 16 | 0
Musculoskeletal and connective tissue disorders
Musculoskeletal pain | 68 | 1.8
Joint swelling | 11 | 0
Eye disorders
Vitreoretinal disorders [Includes: chorioretinopathy, detachment of retinal pigment epithelium, macular fibrosis, macular hole, maculopathy, retinal detachment, retinal drusen, retinal vein occlusion, retinopathy, serous retinal detachment, serous retinopathy, subretinal fluid, vitreous detachment, and vitreous floaters] | 37 | 3.5
Visual impairment [Includes: asthenopia, astigmatism, halo vision, metamorphopsia, photophobia, photopsia, vision blurred, visual field defect, and visual impairment] | 35 | 0
Dry eye | 12 | 0
Respiratory disorders
Dyspnea | 26 | 5.3
Cough | 25 | 0
Nervous system disorders
Dizziness | 23 | 1.8
Headache | 16 | 0
Neuropathy peripheral | 14 | 0
Dysgeusia | 11 | 0
Vascular disorders
Hemorrhage | 23 | 0
Hypertension | 16 | 5.3
Venous thromboembolism | 14 | 5.3
Metabolism and nutrition disorders
Decreased appetite | 18 | 1.8
Infections and infestations
Urinary tract infection | 25 | 3.5
Paronychia | 14 | 1.8
Upper respiratory tract infection | 11 | 0

Clinically relevant adverse reactions in < 10% of patients who received AVMAPKI FAKZYNJA CO-PACK included urticaria and decreased ejection fraction.

Table 4 summarizes the laboratory abnormalities in RAMP-201.

Table 4 Select Laboratory Abnormalities (≥ 10%) in Patients with KRAS-Mutated Recurrent LGSOC who Received AVMAPKI FAKZYNJA CO-PACK in RAMP-201
Laboratory Abnormality | AVMAPKI FAKZYNJA CO-PACK
 | All Grades (%) [The denominator used to calculate the rate varied from 45 to 57 based on the number of patients with a baseline value and at least one post-treatment value.] | Grade 3 or 4 (%)
Chemistry
Increased creatine phosphokinase | 82 | 19
Increased aspartate aminotransferase | 70 | 3.5
Decreased albumin | 70 | 0
Increased alanine aminotransferase | 58 | 3.5
Increased blood bilirubin | 48 | 3.5
Increased triglycerides | 46 | 3.5
Increased alkaline phosphatase | 37 | 1.8
Decreased potassium | 23 | 9
Hematology
Decreased hemoglobin | 65 | 5
Decreased lymphocyte count | 40 | 1.8
Decreased platelet count | 35 | 0
Decreased neutrophil count | 25 | 1.8
Urine
Proteinuria | 22 | 4.4

Clinically relevant laboratory abnormalities in < 10% of patients who received AVMAPKI FAKZYNJA CO-PACK included increased INR and prolonged activated partial thromboplastin time.

7 DRUG INTERACTIONS

7.1 Effect of Other Drugs on AVMAPKI FAKZYNJA CO-PACK

Strong and Moderate CYP3A4 Inhibitors

Avoid concomitant use of AVMAPKI FAKZYNJA CO-PACK with strong or moderate CYP3A4 inhibitors.

Defactinib is a CYP3A4 substrate. Concomitant use of defactinib with a strong CYP3A4 inhibitor increases defactinib exposure [see Clinical Pharmacology (12.3)], which may increase the risk of AVMAPKI FAKZYNJA CO-PACK adverse reactions.

Strong and Moderate CYP3A4 Inducers

Avoid concomitant use of AVMAPKI FAKZYNJA CO-PACK with strong or moderate CYP3A4 inducers.

Defactinib is a CYP3A4 substrate. Concomitant use of defactinib with a strong CYP3A4 inducer decreases defactinib exposure, which may reduce the effectiveness of FAKZYNJA [see Clinical Pharmacology (12.3)].

Gastric Acid Reducing Agents

Avoid concomitant use of AVMAPKI FAKZYNJA CO-PACK with proton pump inhibitors (PPIs) or H2 receptor antagonists. If concomitant use of an acid-reducing agent cannot be avoided, administer FAKZYNJA 2 hours before or 2 hours after the administration of a locally acting antacid.

Concomitant use of FAKZYNJA with gastric acid reducing agents decreases defactinib exposure, which may reduce the effectiveness of AVMAPKI FAKZYNJA CO-PACK [see Clinical Pharmacology (12.3)].

7.2 Effect of AVMAPKI FAKZYNJA CO-PACK on Other Drugs

Warfarin

Avoid concomitant use of AVMAPKI FAKZYNJA CO-PACK with warfarin. For patients requiring anticoagulation, an alternative to warfarin is recommended. If concomitant use is unavoidable, monitor INR frequently during treatment with AVMAPKI FAKZYNJA CO-PACK.

Cases of bleeding and increased INR occurred in patients taking FAKZYNJA concomitantly with warfarin in clinical trials.

8 USE IN SPECIFIC POPULATIONS

8.1 Pregnancy

Risk Summary

Based on the mechanisms of action, AVMAPKI FAKZYNJA CO-PACK can cause fetal harm when administered to a pregnant woman [see Clinical Pharmacology (12.1)]. There are no available data on the use of AVMAPKI FAKZYNJA CO-PACK in pregnant women to inform a drug-associated risk. Animal reproductive and developmental toxicity studies have not been conducted with avutometinib or defactinib; however, inhibition of either molecular pathway has been associated with embryo-fetal anomalies and lethality in animals. Advise pregnant women and females of reproductive potential of the potential risk to a fetus.

The background risk of major birth defects and miscarriage for the indicated population is unknown. In the U.S. general population, the estimated background risk of major birth defects and miscarriage in clinically recognized pregnancies is 2 to 4% and 15 to 20%, respectively.

8.2 Lactation

Risk Summary

There are no data on the presence of avutometinib, defactinib, or their metabolites in human milk, the effects on the breastfed child, or the effects on milk production. Because of the potential for serious adverse reactions in a breastfed child, advise lactating women not to breastfeed during treatment with AVMAPKI FAKZYNJA CO-PACK and for 2 weeks after the last dose.

8.3 Females and Males of Reproductive Potential

AVMAPKI FAKZYNJA CO-PACK can cause fetal harm when administered to a pregnant woman [see Use in Specific Populations (8.1)].

Pregnancy Testing

Verify the pregnancy status of females of reproductive potential prior to initiating treatment with AVMAPKI FAKZYNJA CO-PACK.

Contraception

Females

Advise females of reproductive potential to use effective contraception during treatment with AVMAPKI FAKZYNJA CO-PACK and for 1 month after the last dose.

Males

Advise male patients with female partners of reproductive potential to use effective contraception during treatment with AVMAPKI FAKZYNJA CO-PACK and for 4 months after the last dose.

Infertility

Based on animal studies, AVMAPKI FAKZYNJA CO-PACK may impair fertility in females and males of reproductive potential. The effects on fertility were not reversible in animals [see Nonclinical Toxicology (13.1)].

8.4 Pediatric Use

The safety and effectiveness of AVMAPKI FAKZYNJA CO-PACK in pediatric patients has not been established.

8.5 Geriatric Use

Of the 136 patients in clinical studies of AVMAPKI FAKZYNJA CO-PACK, 29% were age 65 years or older. No overall differences in safety were observed between patients age 65 years or older and younger patients. Clinical studies of AVMAPKI FAKZYNJA CO-PACK did not include sufficient numbers of patients aged 65 and over to determine whether they respond differently from younger patients.

11 DESCRIPTION

AVMAPKI FAKZYNJA CO-PACK contains AVMAPKI (avutometinib) capsules co-packaged with FAKZYNJA (defactinib) tablets.

AVMAPKI capsules contain avutometinib, a kinase inhibitor. The chemical name of avutometinib is N-(3-Fluoro-4-{[4-methyl-7-(2-pyrimidinyloxy)-2H-chromen-2-on-3-yl]methyl}-2-pyridyl)-N'-methylsulfamide potassium salt. The molecular formula for avutometinib is C21H17FN5O5S (as potassium salt) and its molecular weight is 509.55. The chemical structure of avutometinib is shown below:

Avutometinib potassium is a white to pale yellow powder. It is practically insoluble in the pH range of 1 to 7 in aqueous media. The pKa is 7.02.

AVMAPKI capsules for oral administration contain 0.8 mg of avutometinib (equivalent to 0.864 mg as the avutometinib potassium salt) with the following inactive ingredients: magnesium stearate and mannitol in a hypromellose capsule shell (carrageenan, hypromellose, potassium chloride, purified water, and titanium oxide) printed with black ink (black iron oxide, butyl alcohol, dehydrated alcohol, isopropyl alcohol, potassium hydroxide, propylene glycol, purified water, shellac, and strong ammonia solution).

FAKZYNJA tablets contain defactinib, a kinase inhibitor. The chemical name of defactinib is N-methyl-4-({4-[({3-methyl(methylsulfonyl)aminopyrazin-2-yl}methyl)amino]-5-(trifluoromethyl)pyrimidin-2-yl}amino)benzamide hydrochloride. The molecular formula for defactinib is C20ClH22F3N8O3S (as hydrochloride [HCl] salt) and its molecular weight is 546.96. The chemical structure of defactinib is shown below:

Defactinib hydrochloride is a white to pale yellow powder. It is very slightly soluble at pH 1 and practically insoluble in the pH range of 4.5 to 6.8 in aqueous media. The pKa is 3.81.

FAKZYNJA tablets are available for oral administration. Each FAKZYNJA tablet contains 200 mg defactinib (equivalent to 214.36 mg as the defactinib hydrochloride salt) and the following inactive ingredients: lactose monohydrate, magnesium stearate, microcrystalline cellulose, and sodium starch glycolate.

12 CLINICAL PHARMACOLOGY

12.1 Mechanism of Action

Avutometinib

Avutometinib is a MEK1 inhibitor. Avutometinib induces the formation of inactive RAF/MEK complexes and prevents phosphorylation of MEK1/2 by RAF. RAF and MEK proteins are regulators of the RAS/RAF/MEK/ERK (MAPK) pathway. Avutometinib inhibited MEK1/2 and ERK1/2 phosphorylation and proliferation of tumor cell lines harboring KRAS mutations. Treatment of cancer cells with avutometinib increased the level of phosphorylated focal adhesion kinase (FAK).

Defactinib

Defactinib is an inhibitor of FAK and proline-rich tyrosine kinase-2 (Pyk2), the two members of the FAK family of nonreceptor tyrosine kinases. Defactinib inhibited FAK autophosphorylation in cancer cells in vitro and in mouse xenograft models.

Avutometinib in combination with defactinib enhanced inhibition of cell proliferation in vitro and anti-tumor activity in mouse tumor models including LGSOC.

12.2 Pharmacodynamics

Avutometinib exposure-response relationships and the time course of pharmacodynamic response have not been fully characterized.

Defactinib exposure-response relationships and the time course of pharmacodynamic response have not been fully characterized.

Cardiac Electrophysiology

At the recommended doses for AVMAPKI FAKZYNJA CO-PACK, a mean increase in the QTc interval >20 msec was not observed. For the 88 patients with PR interval measured in RAMP-201, the mean PR interval increased by 16 msec from baseline to Cycle 1 Day 15 4-hours post dose.

12.3 Pharmacokinetics

The pharmacokinetics of avutometinib and defactinib were studied in healthy subjects and in patients with advanced solid tumors and are presented as mean (%CV) unless otherwise specified.

Avutometinib

Avutometinib exhibits dose proportional increases peak plasma concentrations (Cmax) and area under the concentration time curve (AUC) with a single dose ranging from 0.1 mg to 5 mg (0.03 to 1.6 times the approved recommended dose). No significant accumulation of avutometinib was observed at the recommended dosage.

Defactinib

Defactinib exhibits dose proportional increases in Cmax and AUC with twice daily dosing ranging from 12.5 mg to 450 mg (0.06 to 2.25 times the approved recommended dosage). Defactinib steady-state plasma concentrations are reached in approximately 15 days. Defactinib accumulation is approximately 1.5-fold at the approved recommended dosage.

Absorption

The median time to avutometinib peak plasma concentration (Tmax) under fasted conditions is approximately 2 hours.

The median time to defactinib Tmax under fed conditions is approximately 4 hours.

Effect of Food

No clinically significant differences in avutometinib AUC were observed following administration with a high-fat meal. Avutometinib Cmax was decreased by 29% following administration with a high-fat meal (approximately 900 to 1000 calories, 50% fat).

Defactinib AUC increased by 2.7-fold and Cmax increased by 1.9-fold following administration with a high-fat meal (approximately 900 to 1000 calories, 50% fat).

Distribution

Avutometinib steady state apparent volume of distribution (Vd) is 25 L (19%). Avutometinib human plasma protein binding is 99% in vitro.

Defactinib steady state apparent Vd is 1,560 L (59%). Defactinib human plasma protein binding is 90% in vitro.

Elimination

Avutometinib estimated elimination half-life is 51 hours (28%) and the apparent oral clearance (CL/F) is 0.3 L/h (30%).

Defactinib estimated elimination half-life is 9 hours (171%) and the CL/F is 69 L/h (173%).

Metabolism

Avutometinib is primarily metabolized by CYP3A4 and nonenzymatic degradation.

Defactinib is metabolized primarily by CYP3A4 and CYP2C9. Two major metabolites, N-desmethyl sulfonamide (M2) and N-desmethyl amide (M4), were identified in plasma. M2 and M4 AUCs represent 92% and 28% of defactinib exposure, respectively. M2 is inactive and M4 is equipotent when compared to defactinib.

Excretion

After a single dose of radiolabeled avutometinib 2.4 mg (0.8 times the approved recommended dose), 39% (9.5% unchanged) of the dose was recovered in feces and 52% (3.2% unchanged) in urine.

After a single dose of radiolabeled defactinib 400 mg (2 times the approved recommended dose), 87% (52% unchanged) of the dose was recovered in feces and 7.6% (0.8% unchanged) in urine.

Specific Populations

No clinically significant differences in the pharmacokinetics of avutometinib were observed based on age (21 to 87 years), sex, race (84% White, 3% Black and 2% Asian), body weight (40 to 169 kg), mild and moderate renal impairment (CLcr 30 to 89 mL/min, estimated by Cockcroft-Gault), or mild hepatic impairment (AST > ULN or total bilirubin >1 × ULN to 1.5 × ULN). The effect of severe renal impairment (CLcr < 30 mL/min) or moderate to severe hepatic impairment (AST or ALT ≥ 2.5 × ULN or total bilirubin ≥ 1.5 × ULN) on avutometinib pharmacokinetics is unknown.

No clinically meaningful differences in the pharmacokinetics of defactinib were observed based on age (21 to 87 years), sex, race (82% White, 3% Black and 2% Asian), body weight (40 to 169 kg), mild and moderate renal impairment (CLcr 30 to 89 mL/min), or mild hepatic impairment (AST > ULN or total bilirubin >1 × ULN to 1.5 × ULN). The effect of severe renal impairment (CLcr < 30 mL/min) or moderate to severe hepatic impairment (AST or ALT ≥ 2.5 × ULN or total bilirubin ≥ 1.5 × ULN) on defactinib pharmacokinetics is unknown.

Drug Interaction Studies

Clinical Studies

Strong CYP3A4 Inhibitors:

No clinically significant differences in avutometinib pharmacokinetics were observed when used concomitantly with itraconazole (strong CYP3A4 inhibitor).

Defactinib Cmax increased by 2.2-fold and AUC by 3.9-fold following concomitant use with itraconazole (strong CYP3A4 inhibitor) 200 mg daily for 10 days. M4 AUC increased by 2.2-fold and Cmax decreased by 6.8%.

Strong CYP3A4 Inducers:

Avutometinib AUC decreased by 34% with no clinically significant change in Cmax following coadministration with phenytoin (strong CYP3A4 inducer) three times daily for 23 days and a single dose of avutometinib 2.4 mg (0.8 times the approved recommended dose) on Day 17.

Defactinib Cmax decreased by 83% and AUC by 87% following coadministration with phenytoin (strong CYP3A4 inducer) three times daily for 23 days and a single dose of defactinib 200 mg (1.0 times the approved recommended dose) on Day 14. M4 AUC decreased by 79% and Cmax decreased by 70%.

Proton Pump Inhibitors (PPIs):

Defactinib displayed pH-dependent aqueous solubility [see Description (11)]. Defactinib AUC decreased by 79% and Cmax decreased by 85% following concomitant use of multiple doses of omeprazole (PPI) 40 mg daily. M4 AUC decreased by 83% and Cmax decreased by 88%.

In Vitro Studies

CYP450 Enzymes:

Avutometinib is a CYP3A4 substrate, but not a substrate of CYP1A2, CYP2B6, CYP2C8, CYP2C9, CYP2C19, and CYP2D6. Avutometinib is not an inhibitor of CYP3A4, CYP1A2, CYP2B6, CYP2C8, CYP2C9, CYP2C19, and CYP2D6. Avutometinib is not an inducer of CYP3A4, CYP2B6, and CYP1A2.

Defactinib is a CYP3A4 and CYP2C9 substrate, but not a substrate of CYP1A2, CYP2B6, CYP2C8, CYP2C19, and CYP2D6. Defactinib is a reversible inhibitor of CYP3A4 and CYP2C9, but not CYP1A2, CYP2B6, CYP2C8, CYP2C19, and CYP2D6. Defactinib is a time-dependent inhibitor of CYP3A4. Defactinib is an inducer of CYP2B6, and CYP1A2, but not CYP3A4.

UGT Enzymes:

Defactinib may inhibit UGT1A1 at clinically relevant concentrations.

Transporter Systems:

Avutometinib is a substrate of P-gp and BCRP, but not a substrate of MATE1, MATE2-K, OAT1, OAT3, OATP1B1, OATP1B3, OCT1 and OCT2. Avutometinib is not an inhibitor of P-gp, BCRP, MATE1, MATE2-K, OAT1, OAT3, OATP1B1, OATP1B3, OCT1 and OCT2.

Defactinib is a BCRP and P-gp substrate, but not a substrate of MATE1, MATE2-K, OAT1, OAT3, OATP1B1, OATP1B3, OCT1, and OCT2. Defactinib is an inhibitor of P-gp, BCRP, OATP1B1, OATP1B3, and MATE2-K, but not an inhibitor of MATE1, OAT1, OAT3, OCT1, and OCT2.

13 NONCLINICAL TOXICOLOGY

13.1 Carcinogenesis, Mutagenesis, Impairment of Fertility

Avutometinib

Carcinogenesis

Carcinogenicity studies have not been conducted with avutometinib.

Mutagenesis

Avutometinib was not mutagenic in the bacterial reverse mutagenesis (Ames) assay and was not clastogenic in an in vitro Chinese hamster lung chromosome aberration assay or an in vivo rat bone marrow micronucleus assay.

Impairment of Fertility

Dedicated fertility studies have not been conducted with avutometinib. In repeat dose toxicity studies, avutometinib was administered orally once daily for up to 13-weeks duration in rats and monkeys. In female rats, atrophy of the ovary was observed at doses ≥ 0.04 mg/kg/day (approximately ≥ 0.25 times the human exposure at the recommended dose based on AUC). Atrophy of the uterus and thinning of the mucosa and increased single cell necrosis of the mucosal epithelium in the vagina were observed at 0.16 mg/kg/day (0.5 times the human exposure at the recommended dose based on AUC). In female monkeys, thinning of the vaginal mucosa was observed at doses ≥ 0.02 mg/kg/day (≥ 0.7 times the human exposure at the recommended dose based on AUC). All findings were reversible.

Defactinib

Carcinogenesis

Carcinogenicity studies have not been conducted with defactinib.

Mutagenesis

Defactinib was not mutagenic in the bacterial reverse mutagenesis (Ames) assay and was not clastogenic in an in vitro Chinese hamster lung cell chromosome aberration assay. Defactinib was positive in the in vitro micronucleus assay through an aneugenic mechanism and in the in vivo rat bone marrow micronucleus assay.

Impairment of Fertility

Dedicated fertility studies have not been conducted with defactinib. In male rats administered defactinib for up to 13 weeks, small prostate, seminal vesicle, and testes, decreased prostate weight, diffuse tubule degeneration/atrophy of the testes and sperm granuloma of the epididymis were observed at doses ≥ 125 mg/kg/day (below the human exposure at the recommended dose based on AUC). At the end of the recovery period, findings in the testes were observed.

In male dogs administered defactinib for up to 13 weeks, increased prostate and testes weights and testicular degeneration and cellular debris in the epididymis were observed at doses ≥ 1 mg/kg/day (below the human exposure at the recommended dose based on AUC). At the end of the recovery period, findings in the testes and epididymis that included cellular debris, duct dilation, and hypospermia were observed.

13.2 Animal Toxicology and/or Pharmacology

Avutometinib

In repeat-dose toxicity studies up to 13-weeks duration in rats and monkeys, tissue mineralization in multiple organs was observed at doses ≥ 0.01 mg/kg/day and 0.03 mg/kg/day, respectively (≥ 0.06 and 1.4 times the human exposure at the recommended dose based on AUC, respectively) as well as increased inorganic phosphorus in rats.

In a cardiovascular telemetry study in monkeys, a single oral dose of avutometinib increased systolic, diastolic, and mean blood pressure at 1 mg/kg (approximately 15 times the human Cmax at the recommended dose). In the repeat-dose toxicology studies up to 13-weeks duration in rats, myocardial degeneration and necrosis were observed at doses ≥ 0.01 mg/kg/day (below the human exposure at the recommended dose based on AUC).

Defactinib

In a cardiovascular telemetry study in dogs, a single oral dose of defactinib decreased myocardial contractility at doses ≥ 5 mg/kg (approximately the human exposure at the recommended dose based on AUC) and increased ventricular systolic, diastolic and mean blood pressure at doses ≥ 25 mg/kg/day (≥ 2.7 times the human exposure at the recommended dose based on AUC). In the 13-week repeat-dose toxicology study in dogs, myocardium hypertrophy was observed at doses ≥ 1 mg/kg/day (below the human exposure at the recommended dose based on AUC) at the end of the dosing and recovery periods.

14 CLINICAL STUDIES

The efficacy of AVMAPKI FAKZYNJA CO-PACK was evaluated in RAMP-201 (NCT04625270), an open-label, multicenter study that included 57 adult patients with measurable KRAS-mutated recurrent LGSOC. Patients were required to have received at least one prior systemic therapy, including a platinum-based regimen. KRAS mutation status was determined by prospective local testing using next generation sequencing (NGS) or polymerase chain reaction of tumor tissue specimens. Patients were excluded if they were candidates for debulking surgery, were on treatment with warfarin, had an active skin disorder requiring systemic therapy within the past year, or had an ocular disorder (including a history of retinal pathology, an active or chronic visually significant corneal disorder, or a history of glaucoma).

Patients received AVMAPKI 3.2 mg orally twice weekly for the first 3 weeks out of a 4-week cycle and FAKZYNJA 200 mg orally twice daily for the first 3 weeks out of a 4-week cycle until disease progression or unacceptable toxicity. The major efficacy outcome measure was overall response rate (ORR) assessed by blinded independent review committee (BIRC) according to Response Evaluation Criteria in Solid Tumors (RECIST), version 1.1. An additional efficacy outcome measure was duration of response (DoR). Tumor response assessments occurred every 8 weeks for the first 72 weeks and every 12 weeks thereafter.

The median age was 60 years (range: 29 to 87); 75% were White, 3.5% were Asian, 3.5% were Black or African American, and 18% did not have race reported; 3.5% of patients were Hispanic or Latino; 72% had an ECOG PS of 0 and 28% had ECOG PS of 1. The KRAS mutations identified by local testing were G12V (53%), G12D (35%), Q61H (3.5%), G12C (1.8%), G12R (1.8%), A146V (1.8%), and mutations not otherwise specified at G12x (1.8%) and on codon 12/13 (1.8%). Fourteen percent of patients had received 1 prior line of systemic therapy, 25% of patients had received 2 prior lines, 18% had received 3 prior lines and 40% had received more than 3 prior lines of systemic therapy. All patients had received prior platinum-based chemotherapy, 84% received prior hormonal therapy (as maintenance or treatment), 40% received prior bevacizumab and 21% received a prior MEK inhibitor.

Efficacy results are presented in Table 5.

Table 5 Efficacy Results in RAMP-201
 | AVMAPKI FAKZYNJA CO-PACK N = 57
Confirmed Overall Response Rate (95% CI) [ORR 95% CI calculated using Clopper-Pearson method] | 44% (31,58)
Complete response | 3.5%
Partial response | 40%
Duration of Response (DoR)
Range (months) | 3.3, 31.1

The tumor KRAS mutations observed in the 25 responders were A146V, G12D, G12R, G12V, and Q61H.

16 HOW SUPPLIED/STORAGE AND HANDLING

AVMAPKI FAKZYNJA CO-PACK is supplied in a carton that contains:

AVMAPKI capsules in a 24-count bottle with child-resistant closure (NDC 71779-660-02) | NDC 71779-623-01
FAKZYNJA tablets in a 42-count bottle with child-resistant closure (NDC 71779-630-01)

- AVMAPKI (avutometinib) 0.8 mg capsules are supplied as white capsules with "6766" printed on the cap and the strength "0.8 mg" printed on the body in black ink in a bottle containing 24 capsules. The bottle contains a desiccant that should not be discarded.
- FAKZYNJA (defactinib) 200 mg tablets are supplied as white to off-white, oval and debossed with "VS2" on one side of the tablet in a bottle containing 42 tablets.

STORAGE AND HANDLING

Store AVMAPKI capsules and FAKZYNJA tablets refrigerated at 2°C to 8°C (36°F to 46°F) in their original bottles.

17 PATIENT COUNSELING INFORMATION

Advise the patient to read the FDA-approved patient labeling (Patient Information).

Ocular Toxicities

Inform patients of the need for eye exams before and during treatment with AVMAPKI FAKZYNJA CO-PACK.

Advise patients to contact their healthcare provider if they experience any visual changes, pain, or inflammation around their eye(s) [see Warnings and Precautions (5.1)].

Serious Skin Toxicities

Inform patients that skin reactions have occurred during treatment with AVMAPKI FAKZYNJA CO-PACK.

Advise patients to use prophylactic topical steroids and oral antibiotics [see Dosage and Administration (2.2)] and to limit unnecessary exposure to sunlight with application of daily sunscreen (sun protection factor [SPF] ≥ 30) [see Warnings and Precautions (5.2)].

Advise patients to contact their healthcare provider if they develop a rash, progressively worsening skin reactions, or blistering of the skin or mouth [see Warnings and Precautions (5.2)].

Hepatotoxicity

Advise patients that they will need to undergo laboratory testing to monitor their liver function.

Advise patients to contact their healthcare provider for signs or symptoms of liver dysfunction [see Warnings and Precautions (5.3)].

Rhabdomyolysis

Inform patients that they will need to undergo laboratory testing to monitor CPK levels.

Advise patients to contact their healthcare provider for signs or symptoms of rhabdomyolysis [see Warnings and Precautions (5.4)].

Drug Interactions

Inform patients to avoid concomitant use of AVMAPKI FAKZYNJA CO-PACK with PPIs or H2 receptor antagonists.

Advise patients that if use of an acid reducing agent cannot be avoided, to take FAKZYNJA 2 hours prior to, or 2 hours after, the administration of a locally acting antacid [see Drug Interactions (7.1)].

Embryo-Fetal Toxicity

Advise pregnant women and females of reproductive potential of the potential risk to a fetus.

Advise females to inform their healthcare providers of a known or suspected pregnancy. Advise females of reproductive potential to use effective contraception during treatment with AVMAPKI FAKZYNJA CO-PACK and for 1 month after the last dose. Advise male patients with female partners of reproductive potential to use effective contraception during treatment with AVMAPKI FAKZYNJA CO-PACK and for 4 months after the last dose [see Warnings and Precautions (5.5) and Use in Specific Population (8.1, 8.3)].

Lactation

Advise women not to breastfeed during treatment with AVMAPKI FAKZYNJA CO-PACK and for 2 weeks after the last dose [see Use in Specific Populations (8.2)].

Infertility

Advise males and females of reproductive potential that AVMAPKI FAKZYNJA CO-PACK may impair fertility [see Use in Specific Populations (8.3)].

Manufactured for and Distributed by:
Verastem, Inc.
Needham, Massachusetts 02494
1-877-878-6662

© 2025 Verastem, Inc.

PATIENT INFORMATION
AVMAPKI™ FAKZYNJA™ CO-PACK (ave-MAP-kee Fak-zin-jah koh-pak)
(avutometinib capsules; defactinib tablets)
co-packaged for oral use

What is AVMAPKI FAKZYNJA CO-PACK?
AVMAPKI FAKZYNJA CO-PACK is a prescription medicine used to treat adults who have:

- low-grade serous ovarian cancer (LGSOC) that has come back (recurrent), and
- LGSOC with an abnormal KRAS gene, and
- previously been treated with medicine for their cancer.

It is not known if AVMAPKI FAKZYNJA CO-PACK is safe and effective in children.

Before taking AVMAPKI FAKZYNJA CO-PACK, tell your healthcare provider about all of your medical conditions, including if you:

- have a history of eye or vision problems
- have had severe skin reactions
- have liver problems
- are pregnant or plan to become pregnant. AVMAPKI FAKZYNJA CO-PACK can harm your unborn baby.
  Females who are able to become pregnant:
  - Your healthcare provider should do a pregnancy test before you start treatment with AVMAPKI FAKZYNJA CO- PACK.
  - You should use effective birth control (contraception) during treatment and for 1 month after the last dose of AVMAPKI FAKZYNJA CO-PACK.
  - Tell your healthcare provider right away if you become pregnant or think you may be pregnant during treatment with AVMAPKI FAKZYNJA CO-PACK.
  Males with a female partner who is able to become pregnant:
  - You should use effective birth control (contraception) during treatment and for 4 months after the last dose of AVMAPKI FAKZYNJA CO-PACK.
- are breastfeeding or plan to breastfeed. It is not known if AVMAPKI FAKZYNJA CO-PACK passes into your breast milk. Do not breastfeed during treatment and for 2 weeks after the last dose of AVMAPKI FAKZYNJA CO-PACK.

Tell your healthcare provider about all the medicines you take, including prescription and over-the-counter medicines, vitamins, and herbal supplements. AVMAPKI FAKZYNJA CO-PACK may affect the way other medicines work, and other medicines may affect how AVMAPKI FAKZYNJA CO-PACK works.
Especially tell your healthcare provider if you take:

- proton pump inhibitors (PPIs) or H2 receptor antagonists
- a blood thinner called warfarin

Know the medicines you take. Keep a list of them with you to show your healthcare provider and pharmacist when you get a new medicine.
How should I take AVMAPKI FAKZYNJA CO-PACK?

- Take AVMAPKI FAKZYNJA CO-PACK exactly as directed by your healthcare provider.
- Do not change your dose or stop taking AVMAPKI FAKZYNJA CO-PACK without talking to your healthcare provider.
- If you develop certain side effects your healthcare provider may change your dose, temporarily stop, or completely stop your treatment with AVMAPKI FAKZYNJA CO-PACK.

Take AVMAPKI capsules and FAKZYNJA tablets with food.

- If you vomit after taking AVMAPKI capsules or FAKZYNJA tablets, do not take an additional dose. Take the next scheduled dose as prescribed by your healthcare provider.

AVMAPKI capsules:

- Take each dose at the same time.
- Swallow the capsules whole. Do not chew, break, or open the capsules.
- If you miss a dose of AVMAPKI by more than 24 hours, skip the missed dose and take the next scheduled dose as prescribed by your healthcare provider. Do not take two doses at the same time to make up for a missed dose.

FAKZYNJA tablets:

- Swallow the tablets whole. Do not chew, break, or crush the tablets.
- If you take antacids, take FAKZYNJA tablets 2 hours before or 2 hours after taking the antacid.
- If you miss a dose of FAKZYNJA by more than 6 hours, skip the missed dose and take the next scheduled dose as prescribed by your healthcare provider. Do not take two doses at the same time to make up for a missed dose.

Before and during treatment with AVMAPKI FAKZYNJA CO-PACK, your health care provider will give you medicines to apply to your face, scalp, neck, upper chest and upper back, and antibiotic medicines to take by mouth to help prevent skin reactions.

What should I avoid while taking AVMAPKI FAKZYNJA CO-PACK?

- Limit your time in the sun. AVMAPKI FAKZYNJA CO-PACK can make your skin sensitive to the sun (photosensitivity) and the light from sunlamps and tanning beds. You may burn more easily and get a severe sunburn. Apply daily sunscreen with a Sun Protection Factor (SPF) of 30 or greater and wear a hat and clothes that cover your skin to protect against sunburn. Talk to your healthcare provider if you get a sunburn.

What are the possible side effects of AVMAPKI FAKZYNJA CO-PACK? AVMAPKI FAKZYNJA CO-PACK may cause serious side effects, including:

- eye problems. Eye problems are common with AVMAPKI FAKZYNJA CO-PACK and can be severe. Your healthcare provider will send you to see an eye care professional before starting treatment, during treatment, and for any new or worsening eye problems. Tell your healthcare provider if you get any new or worsening eye problems including:

- changes in vision, such as blurred vision, double vision, or vision loss
- dry eye(s)
- eye and eyelid inflammation, including redness, swelling, and itching

- eye pain
- new or increased floaters (small dark spots or squiggly lines that float across your vision)
- light hurting eyes or seeing flashes of light

- severe skin reactions. Skin reactions are common with AVMAPKI FAKZYNJA CO-PACK and can be severe or life threatening. Tell your healthcare provider if you develop any new or worsening skin reactions including:

- skin rash or acne
- dry skin
- itching

- blisters on your skin
- redness or swelling of your face, hands, or soles of your feet

- blisters or sores in your mouth
- peeling of your skin
- skin infection

- liver problems. Liver problems are common with AVMAPKI FAKZYNJA CO-PACK and can be severe. Treatment with AVMAPKI FAKZYNJA CO-PACK can increase the level of aspartate aminotransferase, alanine aminotransferase, and bilirubin in your blood. Your healthcare provider will do blood tests before starting each treatment cycle and during treatment to check your liver function. Tell your healthcare provider if you get any signs or symptoms of severe liver problems including:

- yellowing of your skin or the white part of your eyes
- itchy skin
- feeling very tired
- flu-like symptoms

- nausea or vomiting
- upper right side stomach pain
- dark or tea colored urine
- bleeding or bruising more easily than normal

- muscle problems (rhabdomyolysis). AVMAPKI FAKZYNJA CO-PACK may cause muscle problems that can be severe. Treatment with AVMAPKI FAKZYNJA CO-PACK can increase the level of an enzyme in your blood called creatine phosphokinase (CPK) and can be a sign of muscle damage. Your healthcare provider will perform blood tests to check your levels of CPK before starting each treatment cycle and during treatment. Tell your healthcare provider if you get any signs or symptoms of increased CPK including:

- weakness or difficulty moving arms and legs

- muscle or bone aches or pain that does not go away

- dark, red colored urine or decreased urine output

The most common side effects of AVMAPKI FAKZYNJA CO-PACK include:

- nausea
- tiredness
- increased aspartate aminotransferase
- diarrhea
- swelling in the body (edema)

- decreased hemoglobin
- increased alanine aminotransferase
- vomiting
- increased blood bilirubin
- increased triglycerides

- stomach-area pain
- acid reflux
- increased alkaline phosphatase
- decreased platelets
- constipation
- shortness of breath

- cough
- urinary tract infection
- decreased lymphocytes
- decreased neutrophils
- proteinuria

AVMAPKI FAKZYNJA CO-PACK may cause fertility problems in females and males, which may affect your ability to have children. Talk to your healthcare provider if this is a concern for you.
Tell your healthcare provider if you have any side effect that bothers you or that does not go away.
These are not all of the possible side effects of AVMAPKI FAKZYNJA CO-PACK. Call your doctor for medical advice about side effects. You may report side effects to FDA at 1-800-FDA-1088.

How should I store AVMAPKI FAKZYNJA CO-PACK?

- Store AVMAPKI capsules and FAKZYNJA tablets in the refrigerator between 36°F to 46°F (2°C to 8°C) in the original bottles.
- The AVMAPKI capsules and FAKZYNJA tablets come in child-resistant bottles.

Keep AVMAPKI FAKZYNJA CO-PACK and all medicines out of the reach of children.

General information about the safe and effective use of AVMAPKI FAKZYNJA CO-PACK.
Medicines are sometimes prescribed for purposes other than those listed in a Patient Information leaflet. Do not use AVMAPKI FAKZYNJA CO-PACK for a condition for which it was not prescribed. Do not give AVMAPKI FAKZYNJA CO- PACK to other people, even if they have the same symptoms that you have. It may harm them. You can ask your pharmacist or healthcare provider for information about AVMAPKI FAKZYNJA CO-PACK that is written for health professionals.

What are the ingredients in AVMAPKI FAKZYNJA CO-PACK?
AVMAPKI (avutometinib) capsules:
Active ingredient: avutometinib
Inactive ingredients: magnesium stearate, mannitol, black iron oxide, butyl alcohol, dehydrated alcohol, isopropyl alcohol, potassium hydroxide, propylene glycol, purified water, shellac, and strong ammonia solution. The capsule shell contains carrageenan, hypromellose, potassium chloride, purified water, and titanium oxide.
FAKZYNJA (defactinib) tablets:
Active ingredient: defactinib
Inactive ingredients: lactose monohydrate, magnesium stearate, microcrystalline cellulose and sodium starch glycolate.
Manufactured for and Distributed by: Verastem, Inc., Needham, Massachusetts 02494
© 2025 Verastem, Inc.
For more information, go to www.AvmapkiFakzynjaCo-Pack.com or call 1-877-878-6662.

This Patient Information has been approved by the U.S. Food and Drug Administration.

Issued: 05/2025

PRINCIPAL DISPLAY PANEL - Kit Carton

NDC 71779-623-01
Rx only

AVMAPKI™
(avutometinib) capsules
0.8 mg

FAKZYNJA™
(defactinib) tablets
200 mg

CO-PACK

This carton contains:

AVMAPKI™ (avutometinib):
1 bottle of 24 capsules

FAKZYNJA™ (defactinib):
1 bottle of 42 tablets

Prescribing Information

Patient Dosing Card

KEEP REFRIGERATED

VERASTEM™
ONCOLOGY

PRINCIPAL DISPLAY PANEL - 0.8 mg Capsule Bottle Label

NDC 71779-660-02
Rx only

AVMAPKI™
(avutometinib) capsules
0.8 mg

KEEP
REFRIGERATED

24 capsules

773622

Recommended Dosage:
See printed Prescribing
Information inside the
carton.

Manufactured for:
Verastem, Inc.
Needham, MA 02494 USA

For information, call toll-free
1-877-878-6662 or visit us at
www.AvmapkiFakzynjaCo-Pack.com

VERASTEM™
ONCOLOGY

© 2025 Verastem, Inc.

PRINCIPAL DISPLAY PANEL - 200 mg Tablet Bottle Label

NDC 71779-630-01
Rx only

FAKZYNJA™
(defactinib) tablets
200 mg

KEEP REFRIGERATED

42 tablets

VERASTEM™
ONCOLOGY

Recommended Dosage: See
printed Prescribing Information
inside the carton.

Manufactured for:
Verastem, Inc.
Needham, MA 02494 USA

For information, call toll-free
1-877-878-6662 or visit us at
www.AvmapkiFakzynjaCo-Pack.com

© 2025 Verastem, Inc.

773624